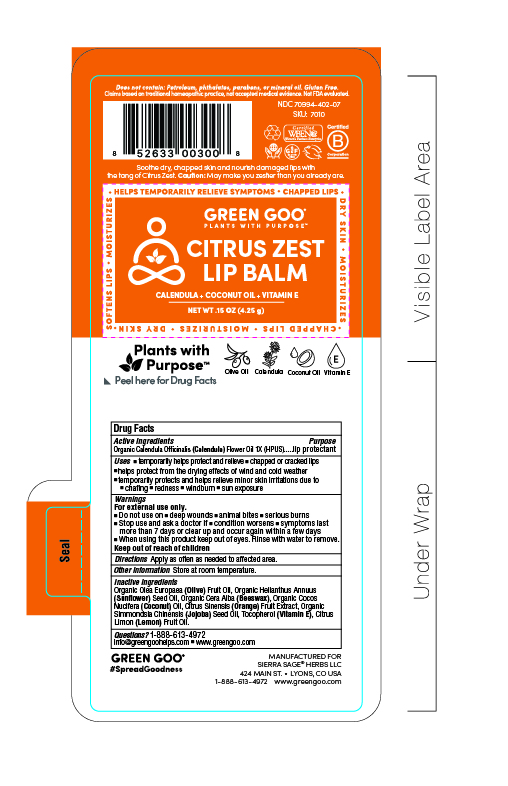 DRUG LABEL: Citrus Zest Lip Balm
NDC: 70994-402 | Form: SALVE
Manufacturer: Spry Life LLC
Category: homeopathic | Type: HUMAN OTC DRUG LABEL
Date: 20251215

ACTIVE INGREDIENTS: CALENDULA OFFICINALIS FLOWER 1 [hp_X]/51.7 g
INACTIVE INGREDIENTS: ORANGE OIL; LEMON OIL; SUNFLOWER OIL; YELLOW WAX; ALPHA-TOCOPHEROL; OLIVE OIL; JOJOBA OIL; COCONUT OIL

Citrus Zest Lip Balm

Purpose Section

Skin Protectant

Active Ingredients

Organic Calendula Officinalis (Calendula) Flowers 1X (HPUS)

Indications & Usage

• temporarily helps relieve • chapped or cracked lips
• helps protect from the drying effects of wind and cold weather
• temporarily protects and helps relieve minor skin irritations due to • chaffing • redness • windburn • sun exposure
• temporarily helps moisturize • chapped and cracked lips

Keep out of reach of children section

Keep out of reach of children.

Warnings Section

Warnings

For external use only.

■ Do not use on ■ deep wounds ■ animal bites ■ serious burns

■ Stop use and ask a doctor if conditions worsens symptoms last more than 7 days or clear up and occur again within a few days

■ When using this product keep out of eyes. rinse with water to remove.

Storage

Store at room temperature.

Dosage & Administration Section

Apply as often as needed to affected area.

Inactive Ingredients

Organic Beeswax (Cera alba), Organic Cocos nucifera (Coconut) Oil, Organic Jojoba (Simmondsia Chinensis) Oil, Organic Helianthus annuus (Sunflower) Oil, Organic Olive (Olea europaea) Oil, Non-GMO (100% Sunflower) Mixed Tocopherols (Vitamin E) Oil. Essential Oils of Sweet Orange and Lemon.